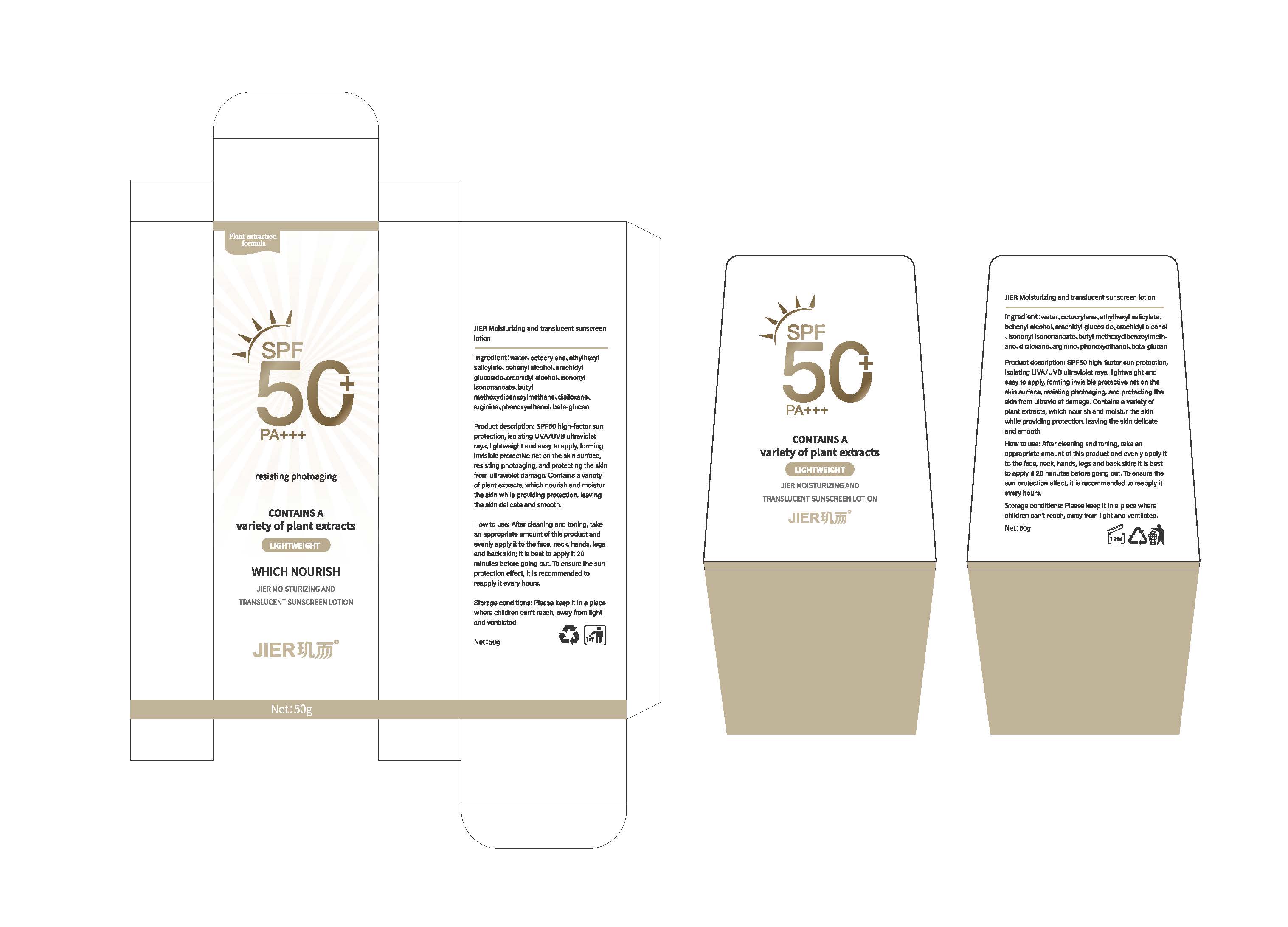 DRUG LABEL: JER Moisturizing and translucent sunscreen
NDC: 85030-001 | Form: LOTION
Manufacturer: Guangdong Dayi Biotechnology Co., Ltd.
Category: otc | Type: HUMAN OTC DRUG LABEL
Date: 20250316

ACTIVE INGREDIENTS: OCTOCRYLENE 2.5 g/50 g; ETHYLHEXYL SALICYLATE 2.5 g/50 g; BUTYL METHOXYDIBENZOYLMETHANE 1.5 g/50 g
INACTIVE INGREDIENTS: PHENOXYETHANOL; WATER; BEHENYL ALCOHOL; ARACHIDYL GLUCOSIDE; ARACHIDYL ALCOHOL; DISILOXANE; ISONONYL ISONONANOATE; ARGININE

active ingredient

Octocrylene
Ethylhexyl Salicylate
Butyl Methoxydibenzoylmethane

Inactive ingrendient

beta-glucan
water
behenyl alcohol
arachidyl glucoside
arachidyl alcohol、
isononylisononanoate、
disiloxane、
arginine、
phenoxyethanol、

Purpose

SPF50 high-factor sunprotection, isolating UVA/UVB ultravioletrays, lightweight and easy to apply, forminginvisible protective net on the skin surface,resisting photoaging, and protecting the skinfrom ultraviolet damage,. Contains a varietyof plant extracts, which nourish and moisturthe skin while providing protection, leavingthe skin delicate and smooth,.

Warning

Ask a doctor before use if you haveSkin sensitization.Skin plastic surgery

Stop use

Ask a doctor before use if you haveSkin sensitization.Skin plastic surgery

keep out of reach of children

Indication

How to use: After cleaning and toning, takean appropriate amount of this product andevenly apply it to the face, neck, hands, legsand back skin; it is best to apply it 20minutes before going out, To ensure the sunprotection effect, it is recommended toreapply it every hours.

Dosage

How to use: After cleaning and toning, takean appropriate amount of this product andevenly apply it to the face, neck, hands, legsand back skin; it is best to apply it 20minutes before going out, To ensure the sunprotection effect, it is recommended toreapply it every hours.

WHEN USING

it is best to apply it 20minutes before going out, To ensure the sunprotection effect, it is recommended toreapply it every hours.